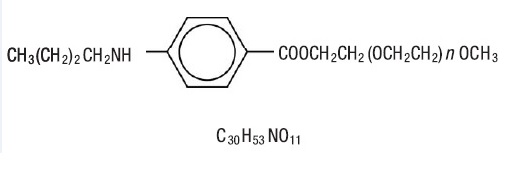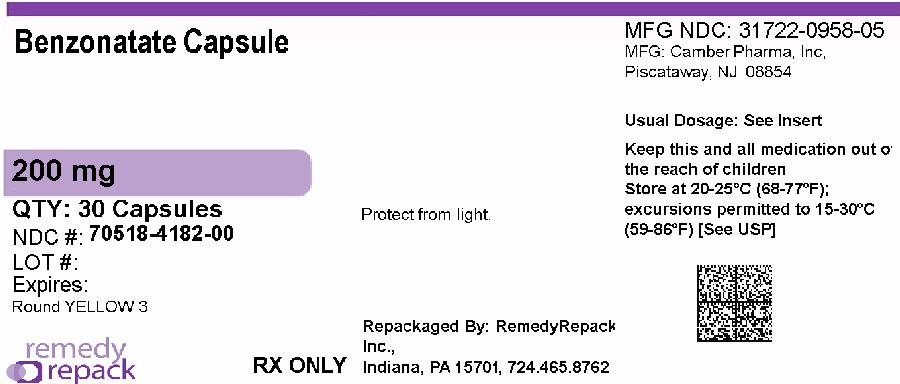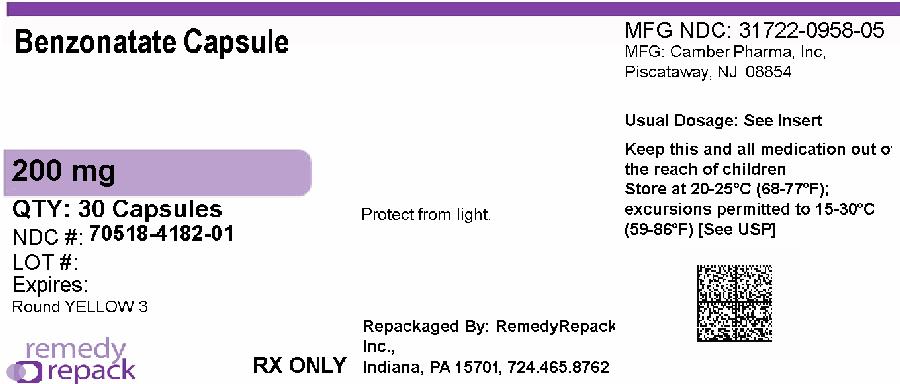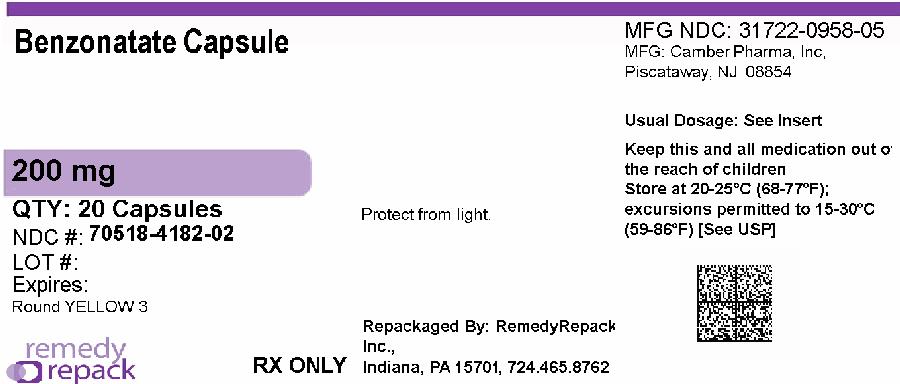 DRUG LABEL: Benzonatate
NDC: 70518-4182 | Form: CAPSULE
Manufacturer: REMEDYREPACK INC.
Category: prescription | Type: HUMAN PRESCRIPTION DRUG LABEL
Date: 20260210

ACTIVE INGREDIENTS: BENZONATATE 200 mg/1 1
INACTIVE INGREDIENTS: GELATIN; WATER; GLYCERIN; MEDIUM-CHAIN TRIGLYCERIDES; LECITHIN, SOYBEAN; ISOPROPYL ALCOHOL; NITROGEN; D&C YELLOW NO. 10; FERROSOFERRIC OXIDE; PROPYLENE GLYCOL; HYPROMELLOSES

BENZONATATE CAPSULES
100 mg Capsules
150 mg Capsules
200 mg Capsules
(benzonatate, USP)

DESCRIPTION

Benzonatate, a non-narcotic oral antitussive agent, is 2, 5, 8, 11, 14, 17, 20, 23, 26-nonaoxaoctacosan-28-yl p-(butylamino) benzoate; with a molecular weight of 603.7.

Each benzonatate capsule USP contains:

Benzonatate, USP 100 mg

Each benzonatate capsule USP contains:

Benzonatate, USP 150 mg

Each benzonatate capsule USP contains:

Benzonatate, USP 200 mg

Benzonatate capsules USP also contain: bloom gelatin, glycerin, purified water, medium chain triglycerides, lecithin, isopropyl alcohol, nitrogen.

100 mg and 200 mg capsules also contain D&C Yellow No. 10.

150 mg capsules also contain FD&C Yellow No. 6 powder.

Each capsule also contains black iron oxide, propylene glycol, hypromellose as imprinting ink.

CLINICAL PHARMACOLOGY

Benzonatate capsules acts peripherally by anesthetizing the stretch receptors located in the respiratory passages, lungs, and pleura by dampening their activity and thereby reducing the cough reflex at its source. It begins to act within 15 to 20 minutes and its effect lasts for 3 to 8 hours. Benzonatate capsules has no inhibitory effect on the respiratory center in recommended dosage.

INDICATIONS AND USAGE

Benzonatate capsules is indicated for the symptomatic relief of cough.

CONTRAINDICATIONS

Hypersensitivity to benzonatate or related compounds.

WARNINGS

Hypersensitivity

Severe hypersensitivity reactions (including bronchospasm, laryngospasm and cardiovascular collapse) have been reported which are possibly related to local anesthesia from sucking or chewing the capsule instead of swallowing it. Severe reactions have required intervention with vasopressor agents and supportive measures.

Psychiatric Effects

Isolated instances of bizarre behavior, including mental confusion and visual hallucinations, have also been reported in patients taking benzonatate capsules in combination with other prescribed drugs.

Accidental Ingestion and Death in Children

Keep benzonatate capsules out of reach of children. Accidental ingestion of benzonatate capsules resulting in death has been reported in children below age 10. Signs and symptoms of overdose have been reported within 15-20 minutes and death has been reported within one hour of ingestion. If accidental ingestion occurs, seek medical attention immediately (see OVERDOSAGE).

PRECAUTIONS

Benzonatate is chemically related to anesthetic agents of the para-amino-benzoic acid class (e.g. procaine; tetracaine) and has been associated with adverse CNS effects possibly related to a prior sensitivity to related agents or interaction with concomitant medication.

Information for patients

Swallow benzonatate capsules whole. Do not break, chew, dissolve, cut, or crush benzonatate capsules. Release of benzonatate from the capsule in the mouth can produce a temporary local anesthesia of the oral mucosa and choking could occur. If numbness or tingling of the tongue, mouth, throat, or face occurs, refrain from oral ingestion of food or liquids until the numbness has resolved. If the symptoms worsen or persist, seek medical attention.

Keep benzonatate capsules out of reach of children. Accidental ingestion resulting in death has been reported in children. Signs and symptoms of overdose have been reported within 15-20 minutes and death has been reported within one hour of ingestion. Signs and symptoms may include restlessness, tremors, convulsions, coma and cardiac arrest. If accidental ingestion occurs, seek medical attention immediately.

Overdosage resulting in death may occur in adults.

Do not exceed a single dose of 200 mg and a total daily dosage of 600 mg. If you miss a dose of benzonatate capsules, skip that dose and take the next dose at the next scheduled time. Do not take 2 doses of benzonatate capsules at one time.

Usage in Pregnancy

Pregnancy Category C

Animal reproduction studies have not been conducted with benzonatate capsules. It is also not known whether benzonatate capsules can cause fetal harm when administered to a pregnant woman or can affect reproduction capacity. Benzonatate capsules should be given to a pregnant woman only if clearly needed.

Nursing mothers

It is not known whether this drug is excreted in human milk. Because many drugs are excreted in human milk caution should be exercised when benzonatate capsules is administered to a nursing woman.

Carcinogenesis, mutagenesis, impairment of fertility

Carcinogenicity, mutagenicity, and reproduction studies have not been conducted with benzonatate capsules.

Pediatric Use

Safety and effectiveness in children below the age of 10 have not been established. Accidental ingestion resulting in death has been reported in children below age 10. Keep out of reach of children.

ADVERSE REACTIONS

Potential Adverse Reactions to benzonatate capsules may include:

Hypersensitivity reactionsincluding bronchospasm, laryngospasm, cardiovascular collapse possibly related to local anesthesia from chewing or sucking the capsule.

CNS:sedation; headache; dizziness; mental confusion; visual hallucinations.

GI:constipation; nausea; GI upset.

Dermatologic:pruritus; skin eruptions.

Other:nasal congestion; sensation of burning in the eyes; vague “chilly” sensation; numbness of the chest; hypersensitivity.

Deliberate or accidental overdose has resulted in death, particularly in children.

OVERDOSAGE

Intentional and unintentional overdose may result in death, particularly in children.

The drug is chemically related to tetracaine and other topical anesthetics and shares various aspects of their pharmacology and toxicology. Drugs of this type are generally well absorbed after ingestion.

Signs and Symptoms

The signs and symptoms of overdose of benzonatate have been reported within 15-20 minutes. If capsules are chewed or dissolved in the mouth, oropharyngeal anesthesia will develop rapidly, which may cause choking and airway compromise.

CNS stimulation may cause restlessness and tremors which may proceed to clonic convulsions followed by profound CNS depression. Convulsions, coma, cerebral edema and cardiac arrest leading to death have been reported within 1 hour of ingestion.

Treatment:

In case of overdose, seek medical attention immediately. Evacuate gastric contents and administer copious amounts of activated charcoal slurry. Even in the conscious patient, cough and gag reflexes may be so depressed as to necessitate special attention to protection against aspiration of gastric contents and orally administered materials. Convulsions should be treated with a short-acting barbiturate given intravenously and carefully titrated for the smallest effective dosage. Intensive support of respiration and cardiovascular-renal function is an essential feature of the treatment of severe intoxication from overdosage.

Do not use CNS stimulants.

DOSAGE AND ADMINISTRATION

Adults and Children over 10 years of age: Usual dose is one 100 mg, 150 mg or 200 mg capsule three times a day as needed for cough. If necessary to control cough, up to 600 mg daily in three divided doses may be given. Benzonatate capsules should be swallowed whole.Benzonatate capsules are not to be broken, chewed, dissolved, cut or crushed.

HOW SUPPLIED

Benzonatate Capsules, USP are available in 200 mg dosage strengths.

The 200 mg capsules are yellow round capsules containing clear to light yellow liquid, printed with ‘3’ sign in black ink.

NDC: 70518-4182-00

NDC: 70518-4182-01

NDC: 70518-4182-02

PACKAGING: 30 in 1 BOTTLE PLASTIC

PACKAGING: 30 in 1 BLISTER PACK

PACKAGING: 20 in 1 BOTTLE PLASTIC

Store at 20°C to 25°C (68°F to77°F) [see USP Controlled Room Temperature].

Protect from light. Dispense in tight, light-resistant container as defined in the USP with a child-resistant closure.

Repackaged and Distributed By:

Remedy Repack, Inc.

625 Kolter Dr. Suite #4 Indiana, PA 1-724-465-8762

PACKAGE LABEL

DRUG: Benzonatate

GENERIC: Benzonatate

DOSAGE: CAPSULE

ADMINSTRATION: ORAL

NDC: 70518-4182-0

NDC: 70518-4182-1

NDC: 70518-4182-2

COLOR: yellow

SHAPE: ROUND

SCORE: No score

SIZE: 8 mm

IMPRINT: 3

PACKAGING: 30 in 1 BOTTLE, PLASTIC

PACKAGING: 30 in 1 BLISTER PACK

PACKAGING: 20 in 1 BOTTLE PLASTIC

ACTIVE INGREDIENT(S):

- BENZONATATE 200mg in 1

INACTIVE INGREDIENT(S):

- GELATIN
- WATER
- GLYCERIN
- MEDIUM-CHAIN TRIGLYCERIDES
- LECITHIN, SOYBEAN
- ISOPROPYL ALCOHOL
- NITROGEN
- D&C YELLOW NO. 10
- FERROSOFERRIC OXIDE
- PROPYLENE GLYCOL
- HYPROMELLOSES